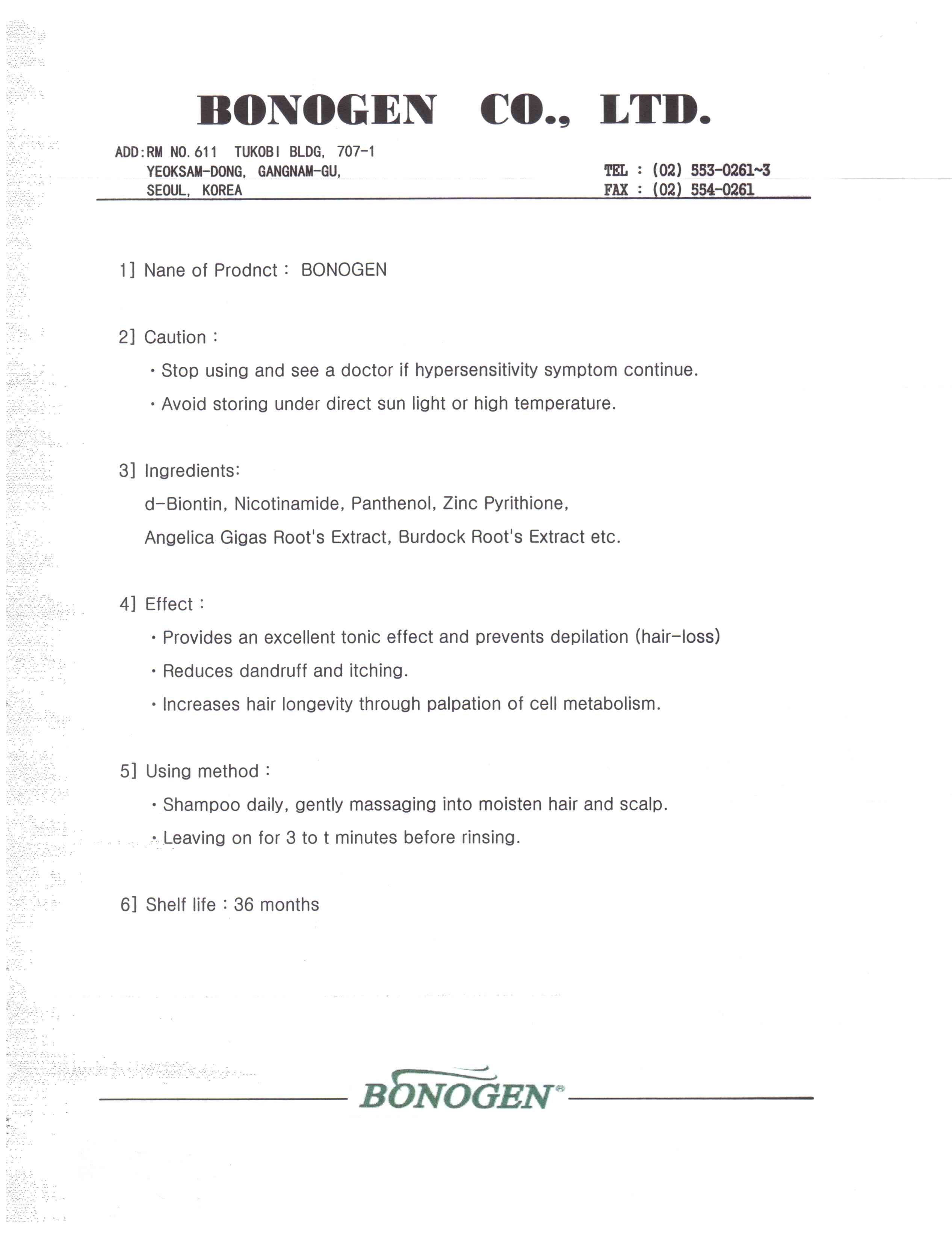 DRUG LABEL: Bonogen Activator
NDC: 50653-3001 | Form: LIQUID
Manufacturer: Bonogen Co., Ltd
Category: otc | Type: HUMAN OTC DRUG LABEL
Date: 20100425

ACTIVE INGREDIENTS: BIOTIN 0.002 mL/1 mL

Drug Facts

Active Ingredient: Biotin

DESCRIPTION

* Bonogen Activator (Hair Loss Treatment) *
1) Name of Product : Bonogen Activator (Hair Loss Treatment)
2) Caution :
· Stop using and see a doctor if any hypersensitivity symptom continues.
· Avoid storing under direct sun light or high temperature.
3) Effect :
· Provides an excellent tonic effect and prevents hair-loss.
· Increases hair longevity through palpation of cell metabolism.
4) Using method :
· Spray Bonogen Activator on the scalp 2~3 times daily as needed.
Recommendable to apply Bonogen Activator enough on the scalp prior
to going to bed.
5) Shelf life : 36 months